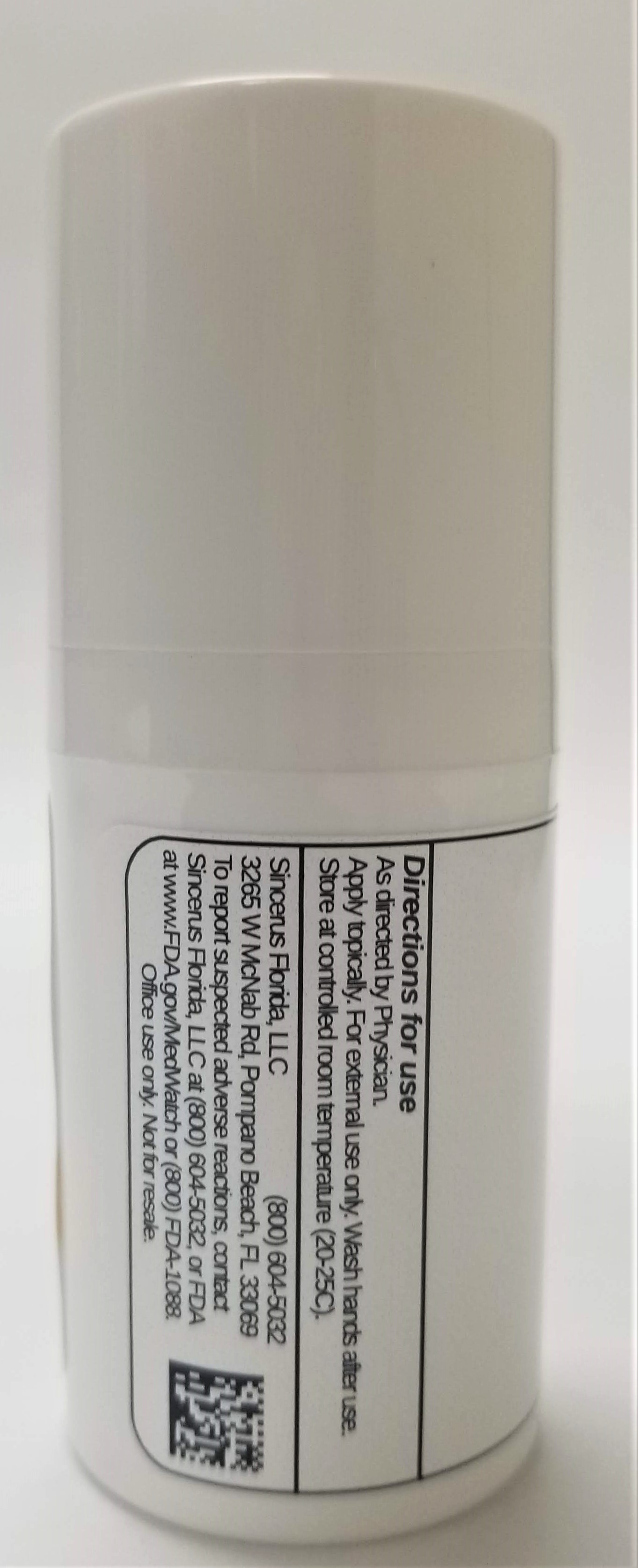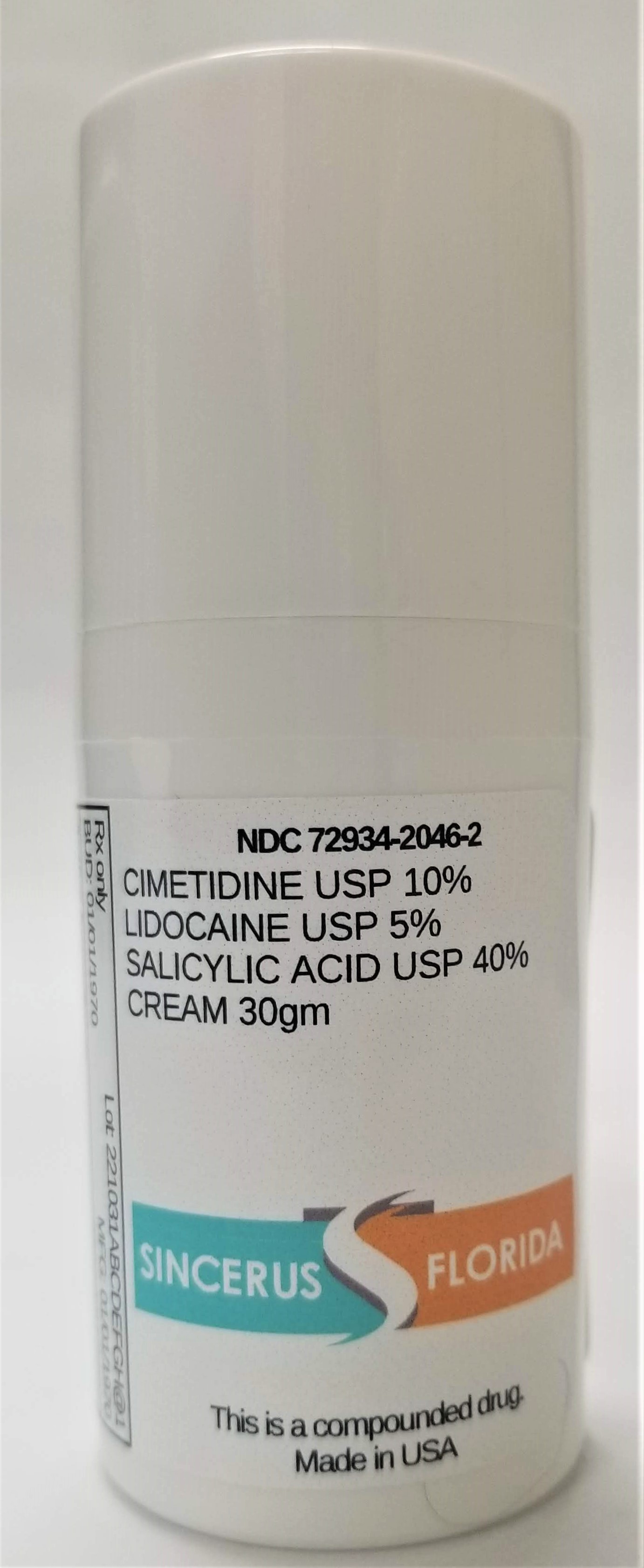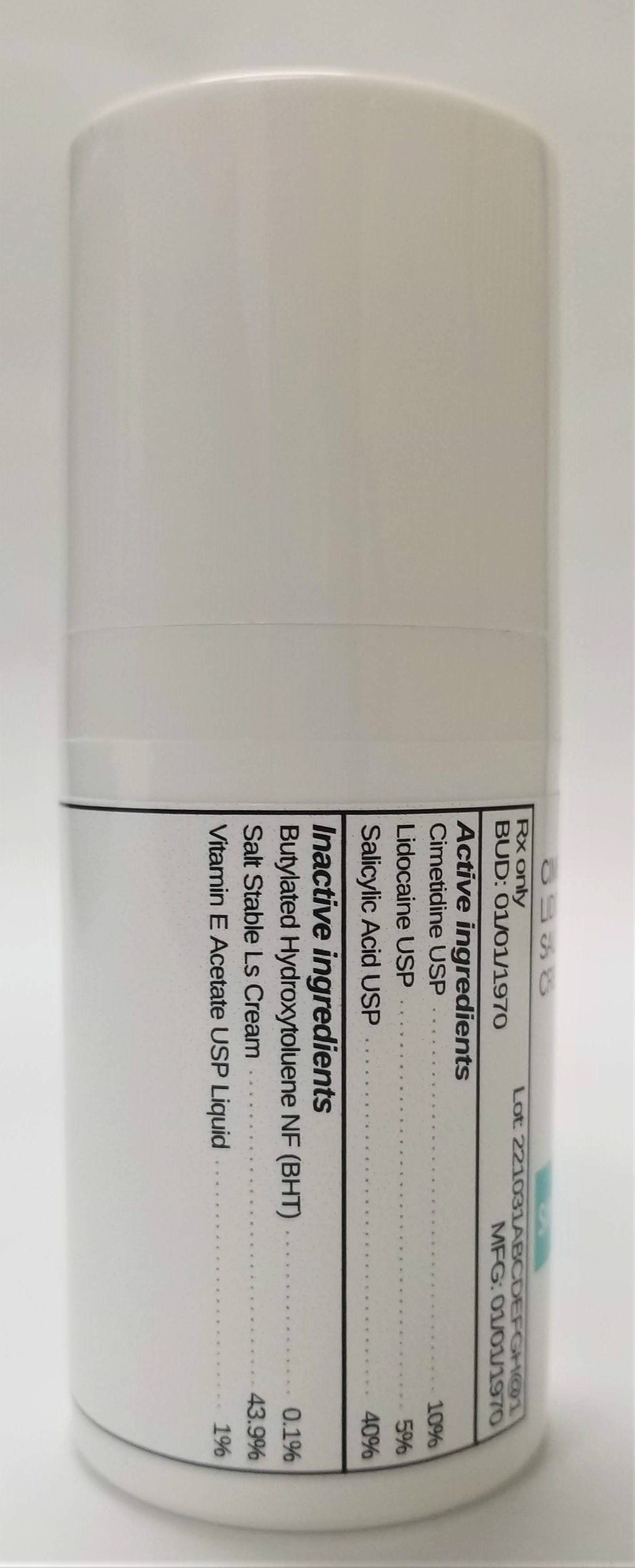 DRUG LABEL: CIMETIDINE 10% / LIDOCAINE 5% / SALICYLIC ACID 40%
NDC: 72934-2046 | Form: CREAM
Manufacturer: Sincerus Florida, LLC
Category: prescription | Type: HUMAN PRESCRIPTION DRUG LABEL
Date: 20190424

ACTIVE INGREDIENTS: SALICYLIC ACID 40 g/100 g; LIDOCAINE 5 g/100 g; CIMETIDINE 10 g/100 g

CIMETIDINE 10% / LIDOCAINE 5% / SALICYLIC ACID 40%